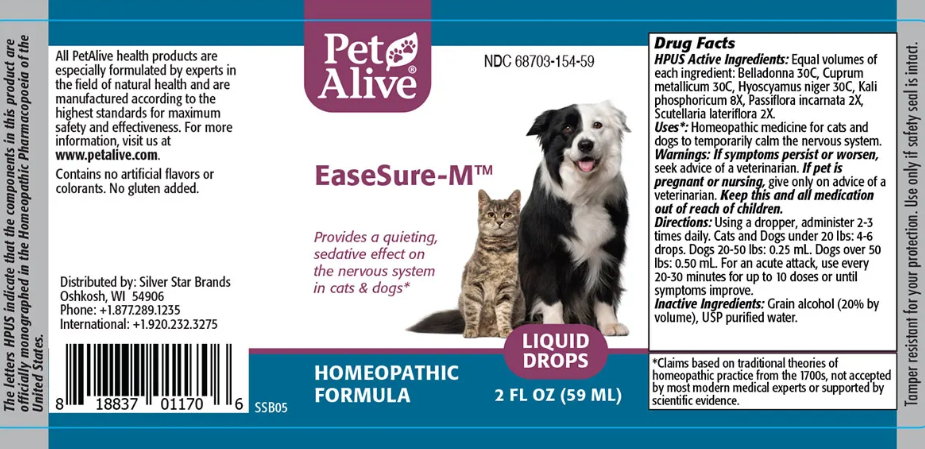 DRUG LABEL: EaseSure-M
NDC: 68703-154 | Form: TINCTURE
Manufacturer: SILVER STAR BRANDS
Category: homeopathic | Type: OTC ANIMAL DRUG LABEL
Date: 20251212

ACTIVE INGREDIENTS: ATROPA BELLADONNA 30 [hp_C]/1 mL; COPPER 30 [hp_C]/1 mL; HYOSCYAMUS NIGER 30 [hp_C]/1 mL; POTASSIUM PHOSPHATE, DIBASIC 8 [hp_X]/1 mL; PASSIFLORA INCARNATA FLOWERING TOP 2 [hp_X]/1 mL; SCUTELLARIA LATERIFLORA 2 [hp_X]/1 mL
INACTIVE INGREDIENTS: ALCOHOL; WATER

EaseSure-M

PURPOSE

Provides a quieting, sedative effect on the nervous system in cats and dogs

ACTIVE INGREDIENT

HPUS Active Ingredients: Equal volumes of each ingredient: Belladonna 30C, Cuprum metallicum 30C, Hyoscyamus niger 30C, Kali phosphoricum 8X, Passiflora incarnata 2X, Scutellaria lateriflora 2X.

INDICATIONS AND USAGE

Uses: Homeopathic medicine for cats and dogs to temporarily calm the nervous system.

WARNINGS

Warnings: If symptoms persist or worsen, seek advice of a veterinarian.

PREGNANCY OR BREAST FEEDING

If pet is pregnant or nursing, give only on advice of a veterinarian.

KEEP OUT OF REACH OF CHILDREN

Keep this and all medication out of reach of children.

DOSAGE AND ADMINISTRATION

Directions: Using a dropper, administer 2-3 times daily. Cats and Dogs under 20 lbs: 4-6 drops. Dogs 20-50 lbs: 0.25 mL. Dogs over 50 Ibs: 0.50 mL. For an acute attack, use every 20-30 minutes for up to 10 doses or until symptoms improve.

INACTIVE INGREDIENT

Inactive Ingredients: grain alcohol (20% by volume), USP purified water

INFORMATION FOR OWNERS/CAREGIVERS

The letter HPUS indicate that the components in this product are officially monographed in the Homeopathic Pharmacopoeia of the United States.

All PetAlive health products are especially formulated by experts in the field of natural health and are manufactured according to the highest standards for maximum safety and effectiveness. For more information, visit us at www.petalive.com.

Distributed by

Distributed by: Silver Star Brands
Oshkosh, WI 54906
Phone: +1.877.289.1235
International: +1.920.232.3275

Contains no artificial flavors or artificial colors. No gluten added

STORAGE AND HANDLING

Tamper resistant for your protection. Use only if safety seal is intact